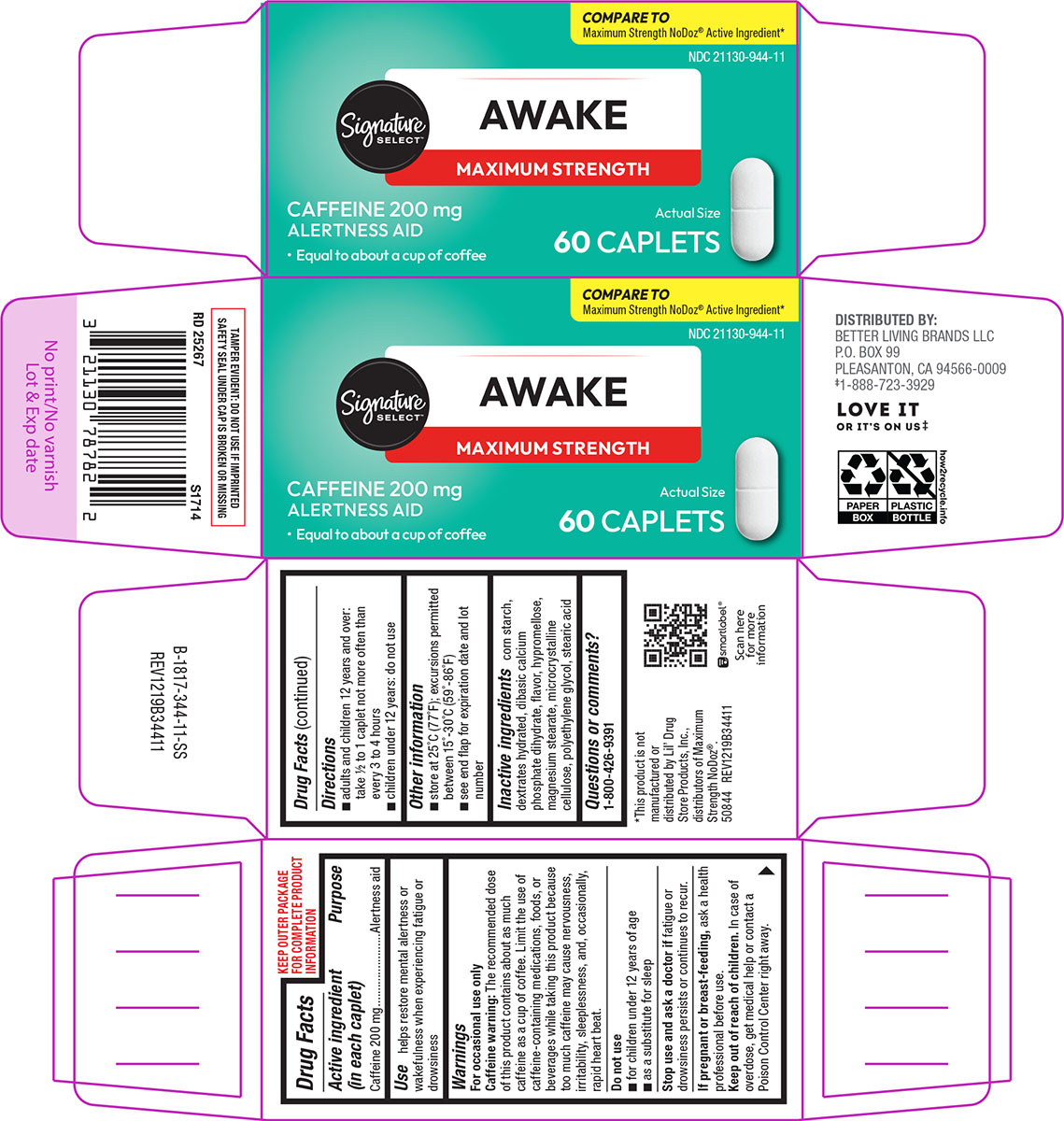 DRUG LABEL: Awake
NDC: 21130-944 | Form: TABLET, FILM COATED
Manufacturer: Better Living Brands, LLC
Category: otc | Type: HUMAN OTC DRUG LABEL
Date: 20260121

ACTIVE INGREDIENTS: CAFFEINE 200 mg/1 1
INACTIVE INGREDIENTS: STARCH, CORN; DEXTROSE MONOHYDRATE; DIBASIC CALCIUM PHOSPHATE DIHYDRATE; HYPROMELLOSE, UNSPECIFIED; MAGNESIUM STEARATE; MICROCRYSTALLINE CELLULOSE; POLYETHYLENE GLYCOL, UNSPECIFIED; STEARIC ACID

Signature Select 44-344

Active ingredient (in each caplet)

Caffeine 200 mg

Purpose

Alertness aid

Use

helps restore mental alertness or wakefulness when experiencing fatigue or drowsiness

Warnings

For occasional use only

Caffeine warning: The recommended dose of this product contains about as much caffeine as a cup of coffee. Limit the use of caffeine-containing medications, foods, or beverages while taking this product because too much caffeine may cause nervousness, irritability, sleeplessness, and, occasionally, rapid heart beat.

Do not use

- for children under 12 years of age
- as a substitute for sleep

Stop use and ask a doctor if

fatigue or drowsiness persists or continues to recur.

If pregnant or breast-feeding,

ask a health professional before use.

Keep out of reach of children.

In case of overdose, get medical help or contact a Poison Control Center right away.

Directions

- adults and children 12 years and over: take 1/2 to 1 caplet not more often than every 3 to 4 hours
- children under 12 years: do not use

Other information

- store at 25°C (77°F); excursions permitted between 15°-30°C (59°-86°F)
- see end flap for expiration date and lot number

Inactive ingredients

corn starch, dextrates hydrated, dibasic calcium phosphate dihydrate, flavor, hypromellose, magnesium stearate, microcrystalline cellulose, polyethylene glycol, stearic acid

Questions or comments?

1-800-426-9391

Principal display panel

COMPARE TO
Maximum Strength NoDoz® Active Ingredient*

NDC 21130-944-11

Signature
Select™

AWAKE
MAXIMUM STRENGTH

CAFFEINE 200 mg
ALERTNESS AID

- Equal to about a cup of coffee

Actual Size

60 CAPLETS

TAMPER EVIDENT: DO NOT USE IF IMPRINTED
SAFETY SEAL UNDER CAP IS BROKEN OR MISSING

*This product is not
manufactured or
distributed by Lil’ Drug
Store Products, Inc.,
distributors of Maximum
Strength NoDoz®.

50844 REV1219B34411

DISTRIBUTED BY:
BETTER LIVING BRANDS LLC
P.O. BOX 99
PLEASANTON, CA 94566-0009
‡1-888-723-3929

LOVE IT
OR IT'S ON US‡

Signature Select 44-344